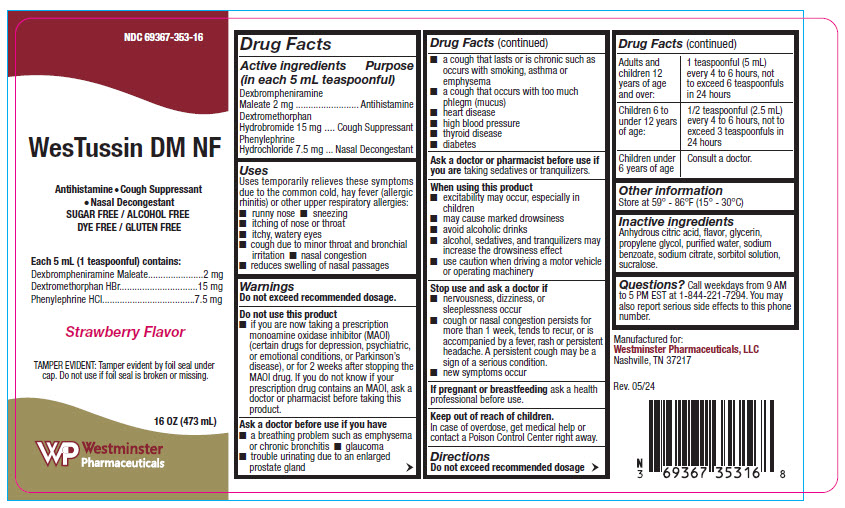 DRUG LABEL: WesTussin DM NF
NDC: 69367-353 | Form: LIQUID
Manufacturer: Westminster Pharmaceuticals, LLC
Category: otc | Type: HUMAN OTC DRUG LABEL
Date: 20240808

ACTIVE INGREDIENTS: PHENYLEPHRINE HYDROCHLORIDE 7.5 mg/5 mL; DEXTROMETHORPHAN HYDROBROMIDE 15 mg/5 mL; DEXBROMPHENIRAMINE MALEATE 2 mg/5 mL
INACTIVE INGREDIENTS: ANHYDROUS CITRIC ACID; GLYCERIN; PROPYLENE GLYCOL; WATER; SODIUM BENZOATE; SORBITOL; SUCRALOSE; TRISODIUM CITRATE DIHYDRATE

WesTussin DM NF

Drug Facts

ACTIVE INGREDIENT

Active ingredients (in each 5 mL teaspoonful) | Purpose
Dexbrompheniramine Maleate 2 mg | Antihistamine
Dextromethorphan Hydrobromide 15 mg | Cough Suppressant
Phenylephrine Hydrochloride 7.5 mg | Nasal Decongestant

Uses

Uses temporarily relieves these symptoms due to the common cold, hay fever (allergic rhinitis) or other upper respiratory allergies:

- runny nose
- sneezing
- itching of nose or throat
- itchy, watery eyes
- cough due to minor throat and bronchial irritation
- nasal congestion
- reduces swelling of nasal passages

Warnings

Do not exceed recommended dosage.

Do not use this product

- if you are now taking a prescription monoamine oxidase inhibitor (MAOI) (certain drugs for depression, psychiatric, or emotional conditions, or Parkinson's disease), or for 2 weeks after stopping the MAOI drug. If you do not know if your prescription drug contains an MAOI, ask a doctor or pharmacist before taking this product.

Ask a doctor before use if you have

- a breathing problem such as emphysema or chronic bronchitis
- glaucoma
- trouble urinating due to an enlarged prostate gland
- a cough that lasts or is chronic such as occurs with smoking, asthma or emphysema
- a cough that occurs with too much phlegm (mucus)
- heart disease
- high blood pressure
- thyroid disease
- diabetes

Ask a doctor or pharmacist before use if you are taking sedatives or tranquilizers.

When using this product

- excitability may occur, especially in children
- may cause marked drowsiness
- avoid alcoholic drinks
- alcohol, sedatives, and tranquilizers may increase the drowsiness effect
- use caution when driving a motor vehicle or operating machinery

Stop use and ask a doctor if

- nervousness, dizziness, or sleeplessness occur
- cough or nasal congestion persists for more than 1 week, tends to recur, or is accompanied by a fever, rash or persistent headache. A persistent cough may be a sign of a serious condition.
- new symptoms occur

PREGNANCY OR BREAST FEEDING

If pregnant or breastfeeding ask a health professional before use.

Keep out of reach of children.

In case of overdose, get medical help or contact a Poison Control Center right away.

Directions

Do not exceed recommended dosage

Adults and children 12 years of age and over: | 1 teaspoonful (5 mL) every 4 to 6 hours, not to exceed 6 teaspoonfuls in 24 hours
Children 6 to under 12 years of age: | 1/2 teaspoonful (2.5 mL) every 4 to 6 hours, not to exceed 3 teaspoonfuls in 24 hours
Children under 6 years of age | Consult a doctor.

Other information

Store at 59° - 86°F (15° - 30°C)

Inactive ingredients

Anhydrous citric acid, flavor, glycerin, propylene glycol, purified water, sodium benzoate, sodium citrate, sorbitol solution, sucralose.

Questions?

Call weekdays from 9 AM to 5 PM EST at 1-844-221-7294. You may also report serious side effects to this phone number.

PRINCIPAL DISPLAY PANEL - 473 mL Bottle Label

NDC 69367-353-16

WesTussin DM NF

Antihistamine • Cough Suppressant
• Nasal Decongestant
SUGAR FREE / ALCOHOL FREE
DYE FREE / GLUTEN FREE

Each 5 mL (1 teaspoonful) contains:
Dexbrompheniramine Maleate
2 mg
Dextromethorphan HBr
15 mg
Phenylephrine HCl
7.5 mg

Strawberry Flavor

TAMPER EVIDENT: Tamper evident by foil seal under
cap. Do not use if foil seal is broken or missing.

16 OZ (473 mL)

Westminster
Pharmaceuticals